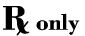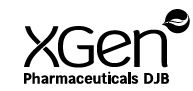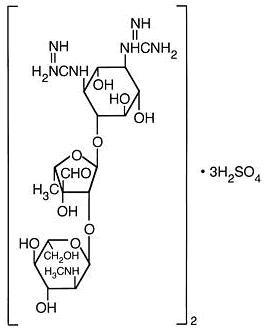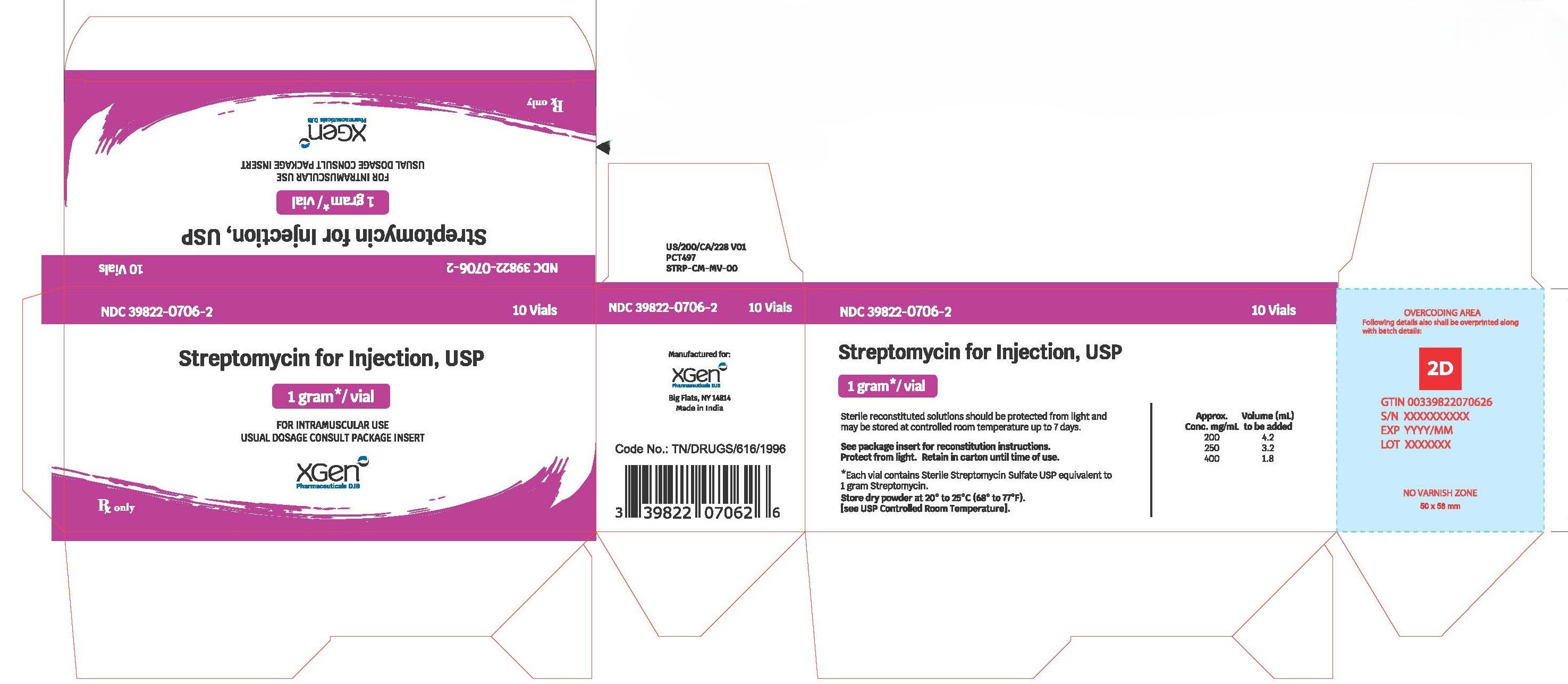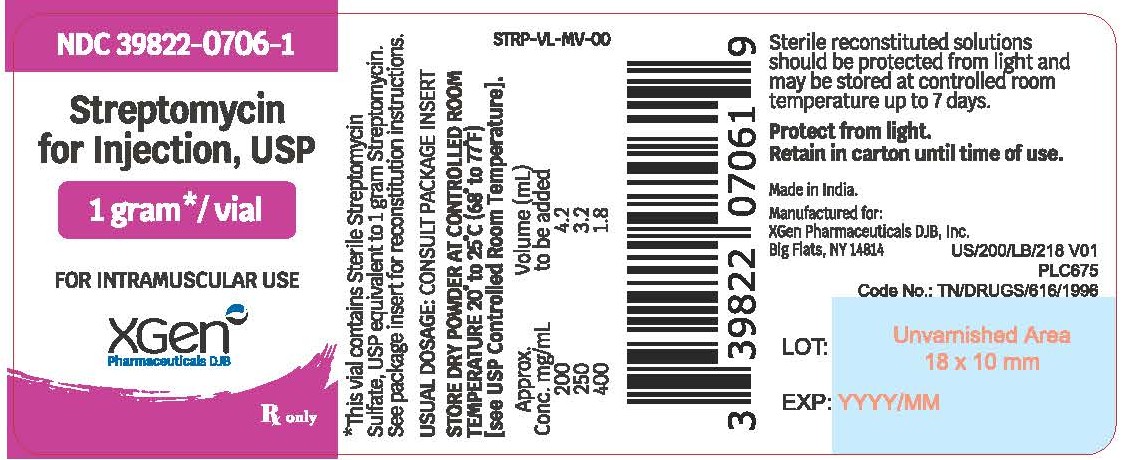 DRUG LABEL: Streptomycin
NDC: 39822-0706 | Form: INJECTION, POWDER, LYOPHILIZED, FOR SOLUTION
Manufacturer: XGen Pharmaceuticals DJB, Inc.
Category: prescription | Type: HUMAN PRESCRIPTION DRUG LABEL
Date: 20260121

ACTIVE INGREDIENTS: STREPTOMYCIN SULFATE 1 g/1 1

Streptomycin for Injection, USP
1 gram*/vial
*Each vial contains Streptomycin Sulfate USP equivalent to 1 gram Streptomycin
For Intramuscular Use

To reduce the development of drug-resistant bacteria and maintain the effectiveness of streptomycin and other antibacterial drugs, streptomycin should be used only to treat or prevent infections that are proven or strongly suspected to be caused by bacteria.

WARNING

THE RISK OF SEVERE NEUROTOXIC REACTIONS IS SHARPLY INCREASED IN PATIENTS WITH IMPAIRED RENAL FUNCTION OR PRE-RENAL AZOTEMIA. THESE INCLUDE DISTURBANCES OF VESTIBULAR AND COCHLEAR FUNCTION, OPTIC NERVE DYSFUNCTION, PERIPHERAL NEURITIS, ARACHNOIDITIS, AND ENCEPHALOPATHY MAY ALSO OCCUR. THE INCIDENCE OF CLINICALLY DETECTABLE, IRREVERSIBLE VESTIBULAR DAMAGE IS PARTICULARLY HIGH IN PATIENTS TREATED WITH STREPTOMYCIN.

RENAL FUNCTION SHOULD BE MONITORED CAREFULLY; PATIENTS WITH RENAL IMPAIRMENT AND/OR NITROGEN RETENTION SHOULD RECEIVE REDUCED DOSES. THE PEAK SERUM CONCENTRATION IN INDIVIDUALS WITH KIDNEY DAMAGE SHOULD NOT EXCEED 20 TO 25 MCG/ML.

THE CONCURRENT OR SEQUENTIAL USE OF OTHER NEUROTOXIC AND/OR NEPHROTOXIC DRUGS WITH STREPTOMYCIN SULFATE, INCLUDING NEOMYCIN, KANAMYCIN, GENTAMICIN, CEPHALORIDINE, PAROMOMYCIN, VIOMYCIN, POLYMYXIN B, COLISTIN, TOBRAMYCIN AND CYCLOSPORINE SHOULD BE AVOIDED.

THE NEUROTOXICITY OF STREPTOMYCIN CAN RESULT IN RESPIRATORY PARALYSIS FROM NEUROMUSCULAR BLOCKAGE, ESPECIALLY WHEN THE DRUG IS GIVEN SOON AFTER THE USE OF ANESTHESIA OR MUSCLE RELAXANTS. THE ADMINISTRATION OF STREPTOMYCIN IN PARENTERAL FORM SHOULD BE RESERVED FOR PATIENTS WHERE ADEQUATE LABORATORY AND AUDIOMETRIC TESTING FACILITIES ARE AVAILABLE DURING THERAPY.

DESCRIPTION

Streptomycin is a water-soluble aminoglycoside derived from Streptomyces griseus. It is marketed as the sulfate salt of streptomycin. The chemical name of streptomycin sulfate is D-Streptamine, O-2-deoxy-2-(methylamino)- α-L-glucopyranosyl-(1→2)- O-5-deoxy-3- C-formyl- α-L-lyxofuranosyl-(1→4)- N,N^1-bis(aminoiminomethyl)-,sulfate (2:3) (salt). The molecular formula for Streptomycin Sulfate is (C21H39N7O12)2 • 3H2SO4 and the molecular weight is 1457.41. It has the following structural formula:

Streptomycin for Injection, equivalent to 1 gram streptomycin/vial, is supplied as a sterile nonpyrogenic lyophilized cake for intramuscular use after reconstitution. The lyophilized cake may reduce to a powder during shipping.

After reconstitution, the pH range for Streptomycin for Injection should be between 4.5 and 7 in a solution containing 200 mg of streptomycin activity per mL.

*Each vial of Streptomycin for Injection contains streptomycin sulfate equivalent to 1 gram of streptomycin.

CLINICAL PHARMACOLOGY

Following intramuscular injection of 1 g of streptomycin as the sulfate, a peak serum level of 25 to 50 mcg/mL is reached within 1 hour, diminishing slowly to about 50 percent after 5 to 6 hours.

Appreciable concentrations are found in all organ tissues except the brain. Significant amounts have been found in pleural fluid and tuberculous cavities. Streptomycin passes through the placenta with serum levels in the cord blood similar to maternal levels. Small amounts are excreted in milk, saliva, and sweat.

Streptomycin is excreted by glomerular filtration. In patients with normal kidney function, between 29% and 89% of a single 600 mg dose is excreted in the urine within 24 hours. Any reduction of glomerular function results in decreased excretion of the drug and concurrent rise in serum and tissue levels.

Microbiology

Streptomycin sulfate is a bactericidal antibiotic. It acts by interfering with normal protein synthesis.

Streptomycin has been shown to be active against most strains of the following organisms both in vitro and in clinical infection. (See INDICATIONS AND USAGE.):

Brucella (brucellosis),
Calymmatobacterium granulomatis (donovanosis, granuloma inguinale),
Escherichia coli, Proteus spp., Aerobacter aerogenes, Klebsiella pneumoniae, and
Enterococcus faecalis in urinary tract infections,
Francisella tularensis,
Haemophilus ducreyi (chancroid),
Haemophilus influenzae (in respiratory, endocardial, and meningeal infections - concomitantly with another antibacterial agent),
Klebsiella pneumoniae pneumonia (concomitantly with another antibacterial agent),
Mycobacterium tuberculosis,
Yersinia pestis,
Streptococcus viridans, Enterococcus faecalis (in endocardial infections - concomitantly with penicillin).

SUSCEPTIBILITY TESTS:

For specific information regarding susceptibility test interpretive criteria and associated test methods and quality control standards recognized by FDA for this drug, please see: https://www.fda.gov/STIC.

INDICATIONS AND USAGE

Streptomycin is indicated for the treatment of individuals with moderate to severe infections caused by susceptibile strains of microorganisms in the specific conditions listed below:

1. Mycobacterium tuberculosis: The Advisory Council for the Elimination of Tuberculosis, the American Thoracic Society, and the Center for Disease Control recommend that either streptomycin or ethambutol be added as a fourth drug in a regimen containing isoniazid (INH), rifampin and pyrazinamide for initial treatment of tuberculosis unless the likelihood of INH or rifampin resistance is very low. The need for a fourth drug should be reassessed when the results of susceptibility testing are known. In the past when the national rate of primary drug resistance to isoniazid was known to be less than 4% and was either stable or declining, therapy with two and three drug regimens was considered adequate. If community rates of INH resistance are currently less than 4%, an initial treatment regimen with less than four drugs may be considered.
Streptomycin is also indicated for therapy of tuberculosis when one or more of the above drugs is contraindicated because of toxicity or intolerance. The management of tuberculosis has become more complex as a consequence of increasing rates of drug resistance and concomitant HIV infection. Additional consultation from experts in the treatment of tuberculosis may be desirable in those settings.

2. Non-tuberculosis infections: The use of streptomycin should be limited to the treatment of infections caused by bacteria which have been shown to be susceptible to the antibacterial effects of streptomycin and which are not amenable to therapy with less potentially toxic agents.

a. Yersinia pestis (plague),
b. Francisella tularensis (tularemia),
c. Brucella,
d. Calymmatobacterium granulomatis (donovanosis, granuloma inguinale),
e. H. ducreyi (chancroid),
f. H. influenzae (in respiratory, endocardial, and meningeal infections-concomitantly with another antibacterial agent),
g. K. pneumoniae pneumonia (concomitantly with another antibacterial agent),
h. E.coli, Proteus, A. aerogenes, K. pneumoniae, and Enterococcus faecalis in urinary tract infections,
i. Streptococcus viridans, Enterococcus faecalis (in endocardial infections - concomitantly with penicillin),
j. Gram-negative bacillary bacteremia (concomitantly with another antibacterial agent).

To reduce the development of drug-resistant bacteria and maintain the effectiveness of streptomycin and other antibacterial drugs, streptomycin should be used only to treat or prevent infections that are proven or strongly suspected to be caused by susceptible bacteria. When culture and susceptibility information are available, they should be considered in selecting or modifying antibacterial therapy. In the absence of such data, local epidemiology and susceptibility patterns may contribute to the empiric selection of therapy.

CONTRAINDICATIONS

A history of clinically significant hypersensitivity to streptomycin is a contraindication to its use. Clinically significant hypersensitivity to other aminoglycosides may contraindicate the use of streptomycin because of the known cross-sensitivity of patients to drugs in this class.

WARNINGS

Ototoxicity

Both vestibular and auditory dysfunction can follow the administration of streptomycin. The degree of impairment is directly proportional to the dose and duration of streptomycin administration, to the age of the patient, to the level of renal function and to the amount of underlying existing auditory dysfunction. The ototoxic effects of the aminoglycosides, including streptomycin, are potentiated by the co-administration of ethacrynic acid, mannitol, furosemide and possibly other diuretics.

The vestibulotoxic potential of streptomycin exceeds that of its capacity for cochlear toxicity. Vestibular damage is heralded by headache, nausea, vomiting and disequilibrium. Early cochlear injury is demonstrated by the loss of high frequency hearing. Appropriate monitoring and early discontinuation of the drug may permit recovery prior to irreversible damage to the sensorineural cells.

Pregnancy

Streptomycin can cause fetal harm when administered to a pregnant woman. Because streptomycin readily crosses the placental barrier, caution in use of the drug is important to prevent ototoxicity in the fetus. If this drug is used during pregnancy, or if the patient becomes pregnant while taking this drug, the patient should be apprised of the potential hazard to the fetus.

Clostridium difficile associated diarrhea

Clostridium difficile associated diarrhea (CDAD) has been reported with use of nearly all antibacterial agents, including Streptomycin for Injection, and may range in severity from mild diarrhea to fatal colitis. Treatment with antibacterial agents alters the normal flora of the colon leading to overgrowth of C. difficile.

C. difficileproduces toxins A and B which contribute to the development of CDAD. Hypertoxin producing strains of C. difficilecause increased morbidity and mortality, as these infections can be refractory to antimicrobial therapy and may require colectomy. CDAD must be considered in all patients who present with diarrhea following antibiotic use. Careful medical history is necessary since CDAD has been reported to occur over two months after the administration of antibacterial agents.

If CDAD is suspected or confirmed, ongoing antibiotic use not directed against C. difficile may need to be discontinued. Appropriate fluid and electrolyte management, protein supplementation, antibiotic treatment of C. difficile, and surgical evaluation should be instituted as clinically indicated.

Risk of Ototoxicity Due to Mitochondrial DNA Variants

Cases of ototoxicity with aminoglycosides have been observed in patients with certain variants in the mitochondrially encoded 12S rRNA gene (MT-RNR1), particularly the m.1555A>G variant. Ototoxicity occurred in some patients even when their aminoglycoside serum levels were within the recommended range. Mitochondrial DNA variants are present in less than 1% of the general US population, and the proportion of the variant carriers who may develop ototoxicity as well as the severity of ototoxicity is unknown. In case of known maternal history of ototoxicity due to aminoglycoside use or a known mitochondrial DNA variant in the patient, consider alternative treatments other than aminoglycosides unless the increased risk of permanent hearing loss is outweighed by the severity of infection and lack of safe and effective alternative therapies.

PRECAUTIONS

General

Prescribing streptomycin in the absence of a proven or strongly suspected bacterial infection or a prophylactic indication is unlikely to provide benefit to the patient and increases the risk of the development of drug-resistant bacteria.

Baseline and periodic caloric stimulation tests and audiometric tests are advisable with extended streptomycin therapy. Tinnitus, roaring noises, or a sense of fullness in the ears indicates need for audiometric examination or termination of streptomycin therapy or both.

Care should be taken by individuals handling Streptomycin for Injection to avoid skin sensitivity reactions. As with all intramuscular preparations, Streptomycin for Injection should be injected well within the body of a relatively large muscle and care should be taken to minimize the possibility of damage to peripheral nerves. (See DOSAGE AND ADMINISTRATION.)

Extreme caution must be exercised in selecting a dosage regimen in the presence of preexisting renal insufficiency. In severely uremic patients a single dose may produce high blood levels for several days and the cumulative effect may produce ototoxic sequelae. When streptomycin must be given for prolonged periods of time, alkalinization of the urine may minimize or prevent renal irritation.

A syndrome of apparent central nervous system depression, characterized by stupor and flaccidity, occasionally coma and deep respiratory depression, has been reported in very young infants in whom streptomycin dosage had exceeded the recommended limits. Thus, infants should not receive streptomycin in excess of the recommended dosage.

In the treatment of venereal infections such as granuloma inguinale, and chancroid, if concomitant syphilis is suspected, suitable laboratory procedures such as a dark field examination should be performed before the start of treatment, and monthly serologic tests should be done for at least four months.

As with other antibiotics, use of this drug may result in overgrowth of nonsusceptible organisms, including fungi. If superinfection occurs, appropriate therapy should be instituted.

Information for Patients

Patients should be counseled that antibacterial drugs including streptomycin should only be used to treat bacterial infections. They do not treat viral infections (e.g., the common cold). When streptomycin is prescribed to treat a bacterial infection, patients should be told that although it is common to feel better early in the course of therapy, the medication should be taken exactly as directed. Skipping doses or not completing the full course of therapy may (1) decrease the effectiveness of the immediate treatment and (2) increase the likelihood that bacteria will develop resistance and will not be treatable by streptomycin or other antibacterial drugs in the future.

Diarrhea is a common problem caused by antibiotics which usually ends when the antibiotic is discontinued. Sometimes after starting treatment with antibiotics, patients can develop watery and bloody stools (with or without stomach cramps and fever) even as late as two or more months after having taken the last dose of the antibiotic. If this occurs, patients should contact their physician as soon as possible.

Drug Interactions

The ototoxic effects of the aminoglycosides, including streptomycin, are potentiated by the coadministration of ethacrynic acid, furosemide, mannitol and possibly other diuretics.

Pregnancy

See WARNINGS section.

Nursing Mothers

Because of the potential for serious adverse reactions in nursing infants from streptomycin, a decision should be made whether to discontinue nursing or to discontinue the drug, taking into account the importance of the drug to the mother.

Pediatric Use

See DOSAGE AND ADMINISTRATION.

ADVERSE REACTIONS

The following reactions are common: vestibular ototoxicity (nausea, vomiting, and vertigo); paresthesia of face; rash; fever; urticaria; angioneurotic edema; and eosinophilia.

The following reactions are less frequent: cochlear ototoxicity (deafness); exfoliative dermatitis; anaphylaxis; azotemia; leucopenia; thrombocytopenia; pancytopenia; hemolytic anemia; muscular weakness; and amblyopia.

Vestibular dysfunction resulting from the parenteral administration of streptomycin is cumulatively related to the total daily dose. When 1.8 to 2 g/day are given, symptoms are likely to develop in the large percentage of patients - especially in the elderly or patients with impaired renal function - within four weeks. Therefore, it is recommended that caloric and audiometric tests be done prior to, during, and following intensive therapy with streptomycin in order to facilitate detection of any vestibular dysfunction and/or impairment of hearing which may occur.

Vestibular symptoms generally appear early and usually are reversible with early detection and cessation of streptomycin administration. Two to three months after stopping the drug, gross vestibular symptoms usually disappear, except from the relative inability to walk in total darkness or on very rough terrain.

Although streptomycin is the least nephrotoxic of the aminoglycosides, nephrotoxicity does occur rarely.

Clinical judgment as to termination of therapy must be exercised when side effects occur.

For medical advice about adverse reactions, contact your medical professional. To report SUSPECTED ADVERSE REACTIONS, contact XGen Pharmaceuticals DJB, Inc. at 1-866-390-4411 or FDA at 1-800-FDA-1088 or www.fda.gov/medwatch.

DOSAGE AND ADMINISTRATION

Intramuscular Route Only

Adults: The preferred site is the upper outer quadrant of the buttock (i.e., gluteus maximus) or the mid-lateral thigh.

Children: It is recommended that intramuscular injections be given preferably in the mid-lateral muscles of the thigh. In infants and small children the periphery of the upper outer quadrant of the gluteal region should be used only when necessary, such as in burn patients, in order to minimize the possibility of damage to the sciatic nerve.

The deltoid area should be used only if well developed, such as in certain adults and older children, and then only with caution to avoid radial nerve injury. Intramuscular injections should not be made into the lower and mid-third of the upper arm. As with all intramuscular injections, aspiration is necessary to help avoid inadvertent injection into a blood vessel.

Injection sites should be alternated. As higher doses or more prolonged therapy with streptomycin may be indicated for more severe or fulminating infections (endocarditis, meningitis, etc.), the physician should always take adequate measures to be immediately aware of any toxic signs or symptoms occurring in the patient as a result of streptomycin therapy.

1. TUBERCULOSIS: The standard regimen for the treatment of drug susceptible tuberculosis has been two months of INH, rifampin and pyrazinamide followed by four months of INH and rifampin (patients with concomitant infection with tuberculosis and HIV may require treatment for a longer period). When streptomycin is added to this regimen because of suspected or proven drug resistance (see INDICATIONS AND USAGE section), the recommended dosing for streptomycin is as follows:

 | Daily | Twice Weekly | Thrice Weekly
Children | 20-40 mg/kg; Max 1 g | 25-30 mg/kg; Max 1.5 g | 25-30 mg/kg; Max 1.5 g
Adults | 15 mg/kg; Max 1 g | 25-30 mg/kg; Max 1.5 g | 25-30 mg/kg; Max 1.5 g

Streptomycin is usually administered daily as a single intramuscular injection. A total dose of not more than 120 g over the course of therapy should be given unless there are no other therapeutic options. In patients older than 60 years of age, the drug should be used at a reduced dosage due to the risk of increased toxicity (See BOXED WARNING).

Therapy with streptomycin may be terminated when toxic symptoms have appeared, when impending toxicity is feared, when organisms become resistant, or when full treatment effect has been obtained. The total period of drug treatment of tuberculosis is a minimum of 1 year; however, indications for terminating therapy with streptomycin may occur at any time as noted above.

2. TULAREMIA: 1 to 2 g daily in divided doses for 7 to 14 days until the patient is afebrile for 5 to 7 days.

3. PLAGUE: 2 grams of streptomycin daily in two divided doses should be administered intramuscularly. A minimum of 10 days of therapy is recommended.

4. BACTERIAL ENDOCARDITIS:
a. Streptococcal endocarditis: in penicillin-sensitive alpha and non-hemolytic streptococcal endocarditis (penicillin MIC ≤0.1 mcg/mL), streptomycin may be used for 2-week treatment concomitantly with penicillin. The streptomycin regimen is 1 g b.i.d. for the first week, and 500 mg b.i.d. for the second week. If the patient is over 60 years of age, the dosage should be 500 mg b.i.d. for the entire 2-week period.

b. Enterococcal endocarditis: Streptomycin in doses of 1 g b.i.d. for 2 weeks and 500 mg b.i.d. for an additional 4 weeks is given in combination with penicillin. Ototoxicity may require termination of the streptomycin prior to completion of the 6-week course of treatment.

5. CONCOMITANT USE WITH OTHER AGENTS:
For concomitant use with other agents to which the infecting organism is also sensitive:
Streptomycin is considered a second-line agent for the treatment of gram-negative bacillary bacteremia, meningitis, and pneumonia; brucellosis; granuloma inguinale; chancroid, and urinary tract infection.

For adults: 1 to 2 grams in divided doses every six to twelve hours for moderate to severe infections. Doses should generally not exceed 2 grams per day.

For children: 20 to 40 mg/kg/day (8 to 20 mg/lb/day) in divided doses every 6 to 12 hours. (Particular care should be taken to avoid excessive dosage in children.)

The dry lyophilized cake is dissolved by adding Water for Injection USP in an amount to yield the desired concentration as indicated in the following table:

Approx. Conc. mg/mL | Volume (mL) of Solvent
200 | 4.2
250 | 3.2
400 | 1.8

Sterile reconstituted solutions should be protected from light and may be stored at room temperature for one week without significant loss of potency.

Parenteral drug products should be inspected visually for particulate matter and discoloration prior to administration, whenever solution and container permit.

HOW SUPPLIED

Streptomycin for Injection, USP is available in vials (NDC 39822-0706-1) containing 1 gram.
Boxes of ten vials use NDC 39822-0706-2.

Store dry powder at 20° to 25°C (68° to 77°F) [see USP Controlled Room Temperature].

PROTECT FROM LIGHT

Manufactured for:
XGen Pharmaceuticals DJB, Inc.
Big Flats, NY 14814

Revised: October 2025
STRP-PI-MV-00
Made in India.

PACKAGE LABEL.PRINCIPAL DISPLAY PANEL

NDC 39822-0706-1
Streptomycin for Injection, USP
1 gram*/ vial
For Intramuscular Use
1 Vial
XGen Pharmaceuticals DJB, Inc.

NDC 39822-0706-2

Streptomycin for Injection, USP
1 gram*/ vial
For Intramuscular Use
Rx Only
10 Vial carton
XGen Pharmaceuticals DJB, Inc.